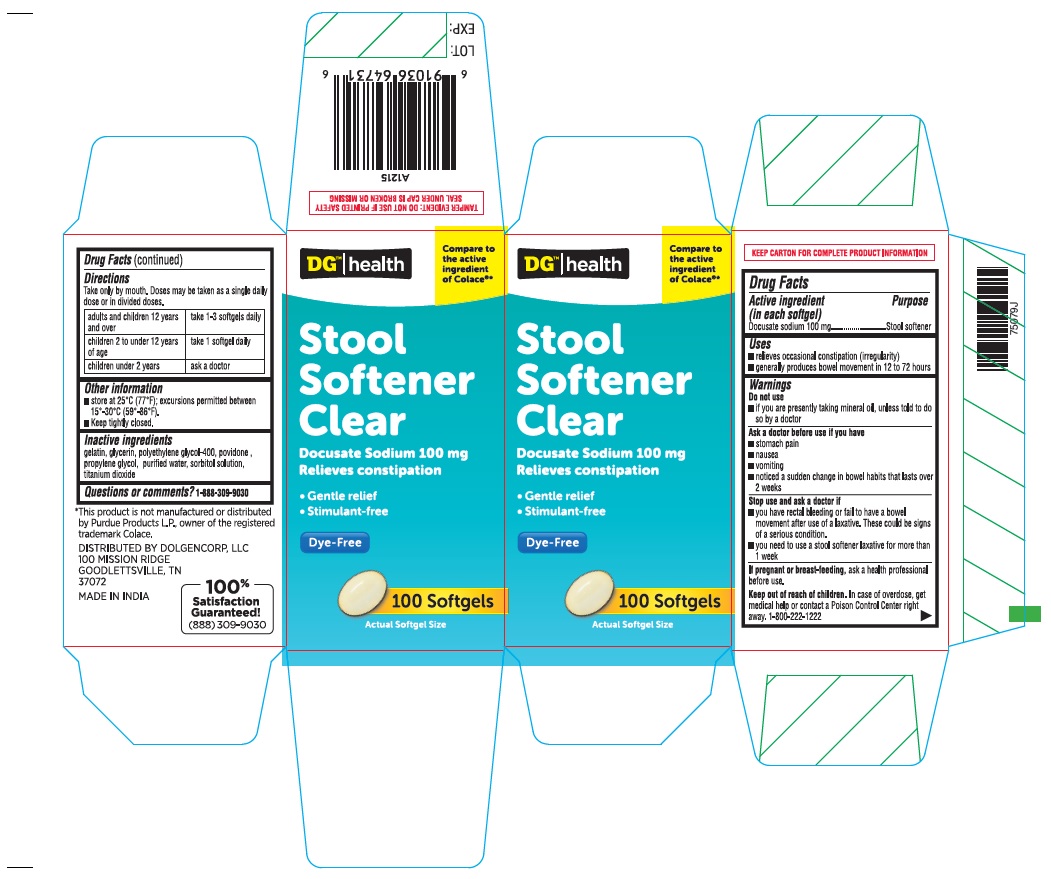 DRUG LABEL: DOCUSATE SODIUM
NDC: 55910-223 | Form: CAPSULE, LIQUID FILLED
Manufacturer: Dolgencorp, Inc.
Category: otc | Type: HUMAN OTC DRUG LABEL
Date: 20241219

ACTIVE INGREDIENTS: DOCUSATE SODIUM 100 mg/1 1
INACTIVE INGREDIENTS: GELATIN; GLYCERIN; POLYETHYLENE GLYCOL 400; POVIDONE K30; PROPYLENE GLYCOL; WATER; SORBITOL; TITANIUM DIOXIDE

DG™ Health Stool Softener Clear

Drug Facts

Active ingredient (in each softgel)

Docusate Sodium 100 mg

Purpose

Stool Softner

Uses

- relieves occasional constipation (irregularity)
- this product generally produces a bowel movement within 12 to 72 hours

Warnings

Do not use

- if you are presently taking mineral oil, unless told to do so by a doctor

Ask a doctor before use if you have

- stomach pain
- nausea
- vomittiong
- a sudden change in bowel habits that lasts more than 2 weeks

Stop use and ask a doctor if

- you have rectal bleeding ot no bowel movement after use of a laxative. These could be signs of a serious condition.
- yo need to use a stool softener laxative for more than 1 week

PREGNANCY OR BREAST FEEDING

If pregnant or breast-feeding,ask a health professional before use

Keep out of reach of children. In case of overdose, get medical help or contact a Poison Control Center right away.1(800)222-1222

Directions

Take only by mouth. Doses may be taken as a single daily dose or in divided doses.

Adults and children 12 years and over : take 1-3 softgels daily.

Children 2 to under 12 years of age : take 1 softgel daily.

Children under 2 years of age: ask a doctor

Other information

- Store at 25°C (77°F), excursions permitted between 15°-30°C (59°-86°F)
- Keep tightly closed.

Inactive ingredients

gelatin, glycerin, polyethylene glycol-400, povidone, propylene glycol, purified water, sorbitol solution, titanium dioxide.

Questions or comments?

1-888-309-9030

PRINCIPAL DISPLAY PANEL

DGTM Health

Compare to the active ingredient of Colace®*

STOOL SOFTENER CLEAR

DOCUSATE SODIUM 100 mg

Relieves constipation

Gentle Relief

Stimulant-Free
Dye-Free

100 Softgels

* This product is not manufactured or distributed by Purdue Products L.P., owner of the registered trademark Colace.